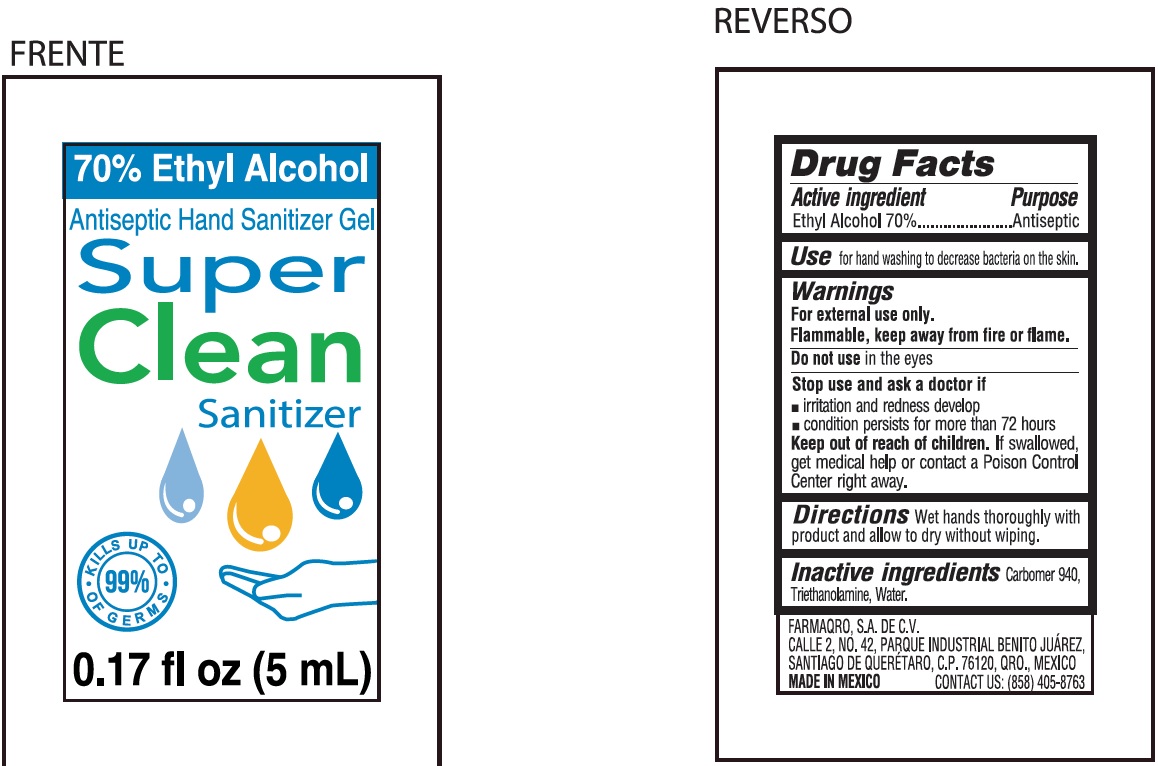 DRUG LABEL: Super Clean Sanitizer
NDC: 62297-000 | Form: GEL
Manufacturer: Farmaqro S.A. de C.V.
Category: otc | Type: HUMAN OTC DRUG LABEL
Date: 20200817

ACTIVE INGREDIENTS: ALCOHOL 0.7 mL/1 mL
INACTIVE INGREDIENTS: CARBOMER HOMOPOLYMER, UNSPECIFIED TYPE; TROLAMINE; WATER

Super Clean Sanitizer

Active ingredient

Ethyl Alcohol 70%

Purpose

Antiseptic

Use

for hand washing to decrease bacteria on the skin.

Warnings

For external use only.

Flammable, keep away from fire or flame.

Do not use

in the eyes

Stop use and ask a doctor if

- irritation and redness develop
- condition persists for more than 72 hours

Keep out of reach of children.

If swallowed, get medical help or contact a Poison Control Center right away.

Directions

wet hands thoroughly with product and allow to dry without wiping.

Inactive ingredients

Carbomer 940, Triethanolamine, Water.